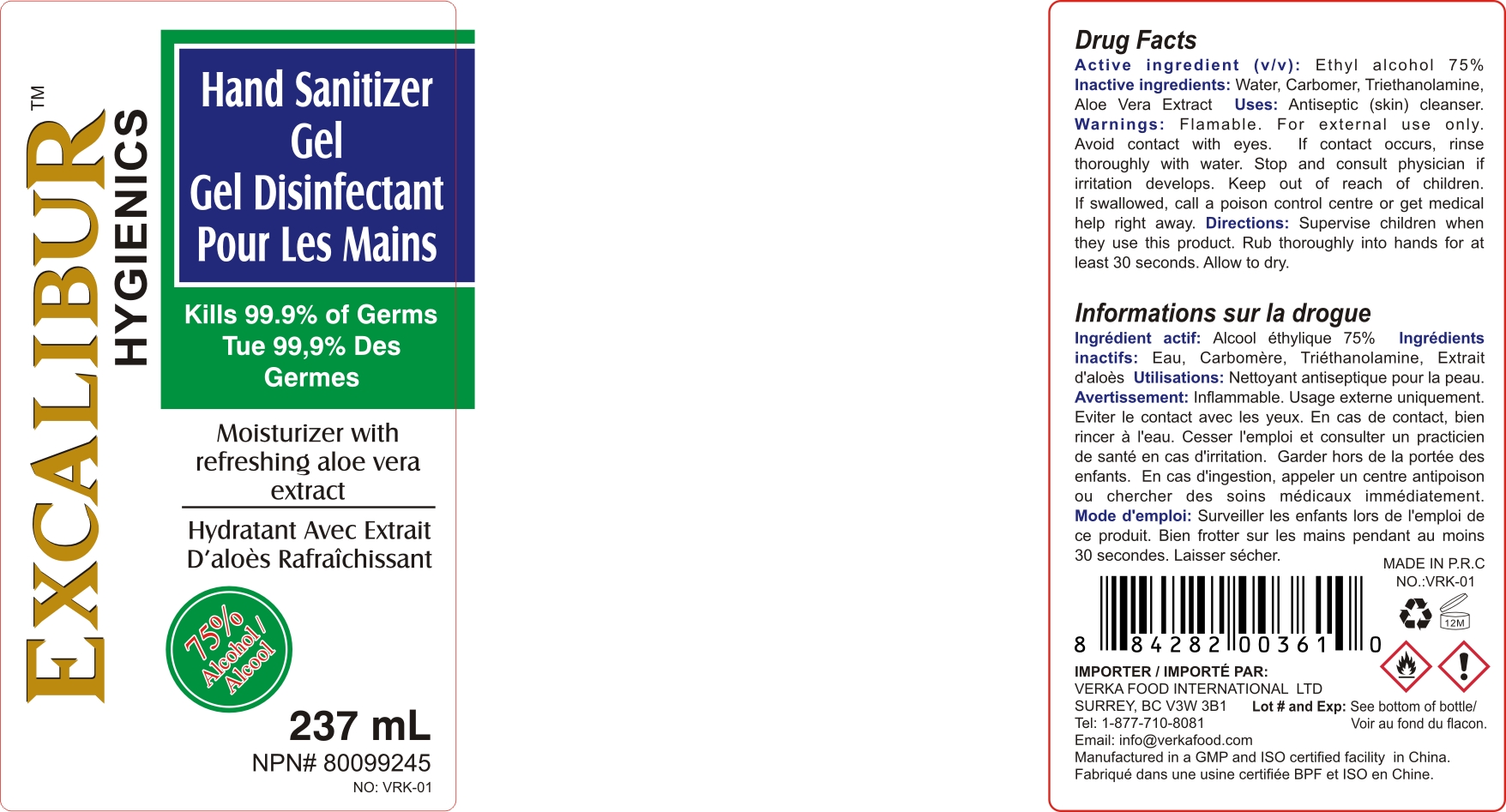 DRUG LABEL: Hand Sanitizer
NDC: 74913-453 | Form: GEL
Manufacturer: SHANTOU S.E.Z BAOJIE INDUSTRY CO., LTD
Category: otc | Type: HUMAN OTC DRUG LABEL
Date: 20200813

ACTIVE INGREDIENTS: ALCOHOL 75 mL/100 mL
INACTIVE INGREDIENTS: ALOE VERA LEAF 0.2 mL/100 mL; TROLAMINE 0.3 mL/100 mL; WATER 24.2 mL/100 mL; CARBOMER 940 0.3 mL/100 mL

EXCALIBUR HAND SANITIZER

Active Ingredient(s)

Alcohol 70% v/v. Purpose: Antiseptic

Purpose

Antiseptic, Hand Sanitizer

Use

Hand Sanitizer to help reduce bacteria that potentially can cause disease. For use when soap and water are not available.

Warnings

For external use only. Flammable. Keep away from heat or flame

Do not use

- in children less than 2 months of age
- on open skin wounds

When using this product keep out of eyes, ears, and mouth. In case of contact with eyes, rinse eyes thoroughly with water.

Stop use and ask a doctor if irritation or rash occurs. These may be signs of a serious condition.

Keep out of reach of children. If swallowed, get medical help or contact a Poison Control Center right away.

Directions

- Place enough product on hands to cover all surface. Rub hands together until dry.
- For Children under 6 years of age, use with supervision

Other information

- Store between 15-30C (59-86F)
- Avoid freezing and excessive heat above 40C (104F)

Inactive ingredients

Water,Carbomer,Triethanolamine,Aloe Vera Extract